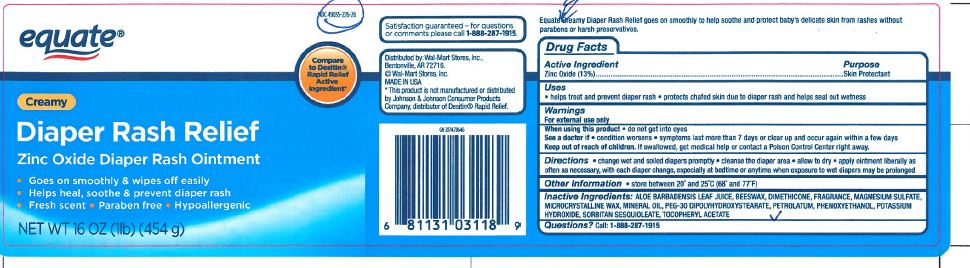 DRUG LABEL: EQUATE CREAMY DIAPER RASH RELIEF
NDC: 49035-319 | Form: CREAM
Manufacturer: Wal-Mart Stores, Inc.
Category: otc | Type: HUMAN OTC DRUG LABEL
Date: 20120301

ACTIVE INGREDIENTS: ZINC OXIDE 59.02 g/454 g
INACTIVE INGREDIENTS: DIMETHICONE; MAGNESIUM SULFATE; MICROCRYSTALLINE WAX; MINERAL OIL; PEG-30 DIPOLYHYDROXYSTEARATE; PETROLATUM; PHENOXYETHANOL; POTASSIUM HYDROXIDE; SORBITAN SESQUIOLEATE

EQUATE CREAMY DIAPER RASH RELIEF

Active Ingredient : Zinc Oxide (13%)

PURPOSE

Uses: Helps treat and prevent diaper rash,protects chafed skin due to diaper rash and helps seal out wetness.

Keep out of reach of children. If swallowed , get medical help or contact a Poison Control Center right away.

Warnings For external use only

INDICATIONS AND USAGE

Direction Change wet and soiled diapers promptly , Cleanse the diaper area , Allow to dry , Apply ointment liberally as often as necessary , With each diaper change , Especially at bedtime or anytime when exposureto wet diapers may be prolonged

INACTIVE INGREDIENT

Inactive Ingredients ; ALOE BARBADENSIS LEAF JUICE, BEESWAX, DIMETHICONE,FRAGRANCE,MAGNESIUM SULFATE,MICORCRYSTALLINE WAX,MINERAL OIL,PEG-30 DIPOLYHYDROXYSTEARATE,PETROLATUM,PHENOXYETHANOL,POTASSIUM HYDROXIDE,SORBITAN SESQUIOLEATE,TOCOPHERYL ACETATE